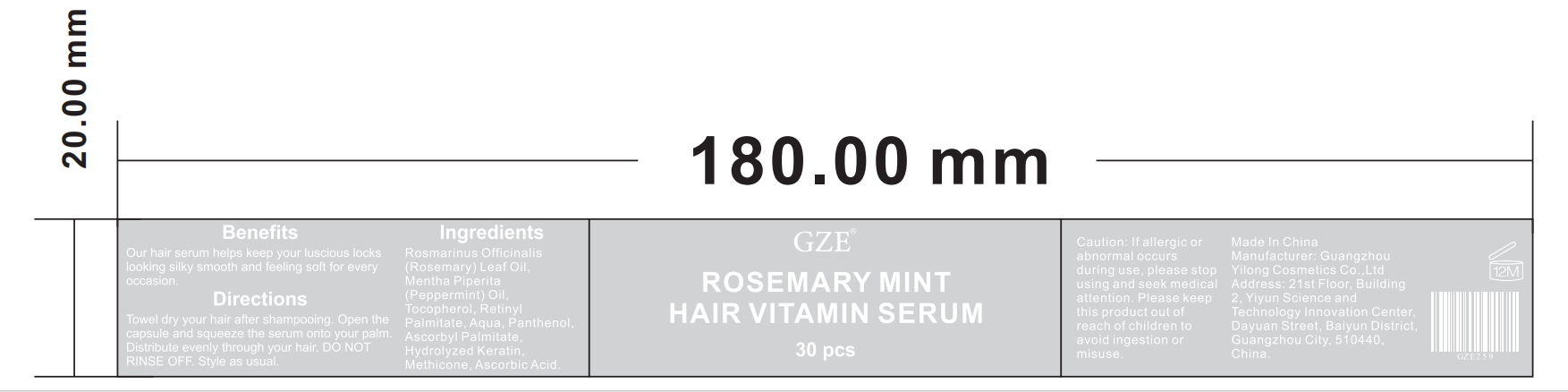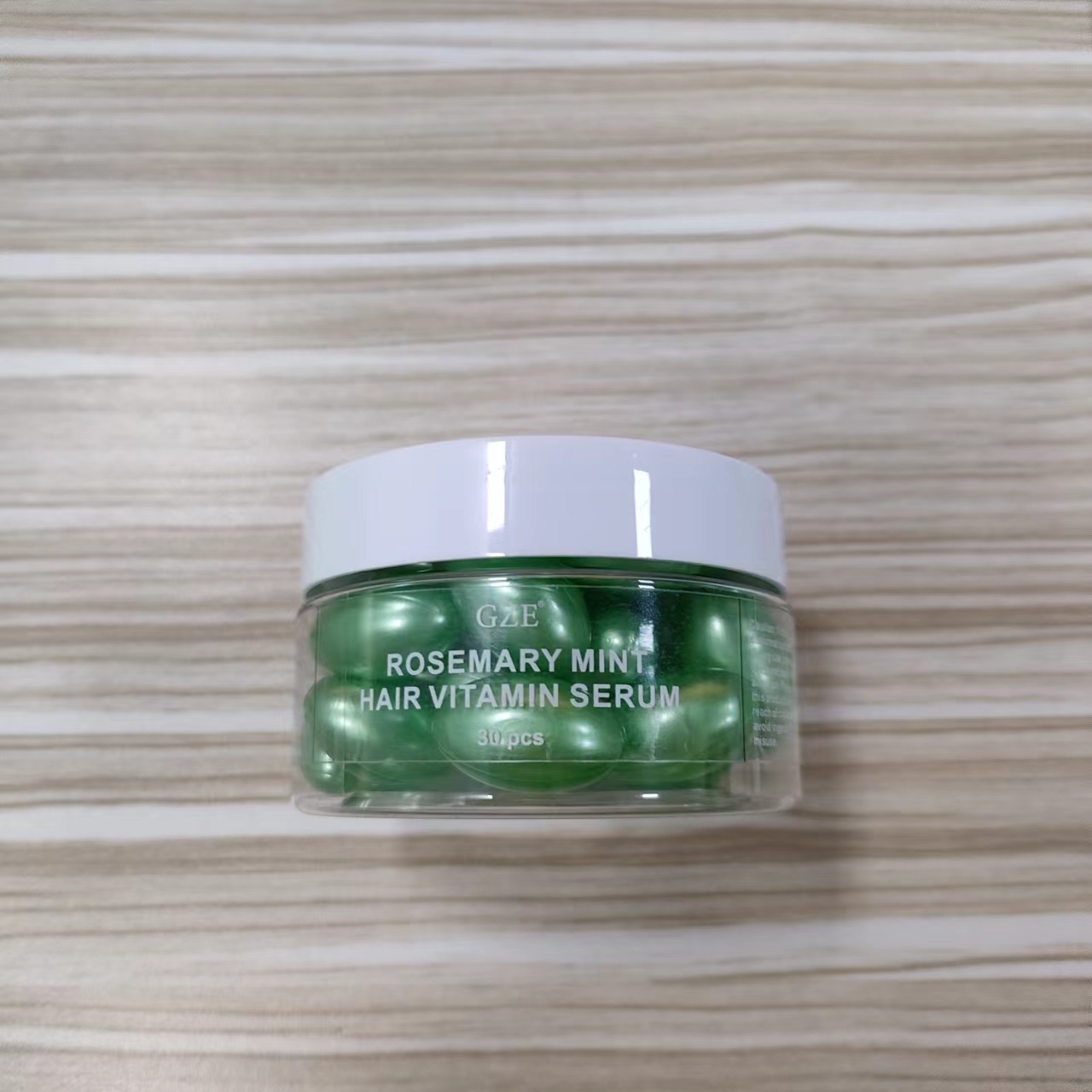 DRUG LABEL: GZE Rosemary Mint Hair VitaminSerum
NDC: 83566-259 | Form: CAPSULE
Manufacturer: Guangzhou Yilong Cosmetics Co., Ltd
Category: otc | Type: HUMAN OTC DRUG LABEL
Date: 20240622

ACTIVE INGREDIENTS: ROSEMARY OIL 40.6 g/100 g
INACTIVE INGREDIENTS: ASCORBIC ACID; COCODIMONIUM HYDROXYPROPYL HYDROLYZED KERATIN (1000 MW); ASCORBYL PALMITATE; TOCOPHEROL; WATER; PEPPERMINT OIL; RETINYL PROPIONATE; METHICONE (20 CST); PANTHENOL

GZE Rosemary Mint Hair VitaminSerum

ACTIVE INGREDIENT

ROSEMARY OIL
RETINYL PROPIONATE
CPEPPERMINT OIL

INDICATIONS AND USAGE

Towel dry your hair after shampooing. Open the capsule and squeeze the serum onto your palm.Distribute evenly through your hair. DO NOTRINSE OFF. Style as usual.

INACTIVE INGREDIENT

ASCORBIC ACID

COCODIMONIUM HYDROXYPROPYL HYDROLYZED KERATIN (1000 MW)

ASCORBYL PALMITATE

TOCOPHEROL

WATER

METHICONE (20 CST)

PANTHENOL

PURPOSE

Our hair serum helps keep your luscious locks looking silky smooth and feeling soft for every occasion.

WARNINGS

For external use only.

Stop use and ask a doctor if rash occurs.

Do not use on damaged or broken skin.

When using this product keep out of eyes. Rinse with water to remove.

Keep out of reach of children. If swallowed, get medical help or contact a Poison Control Center right away.

DOSAGE AND ADMINISTRATION

One at a time (depending on length), cut open the capsule, pour the serum into your hands and apply evenly to the ends of your hair.